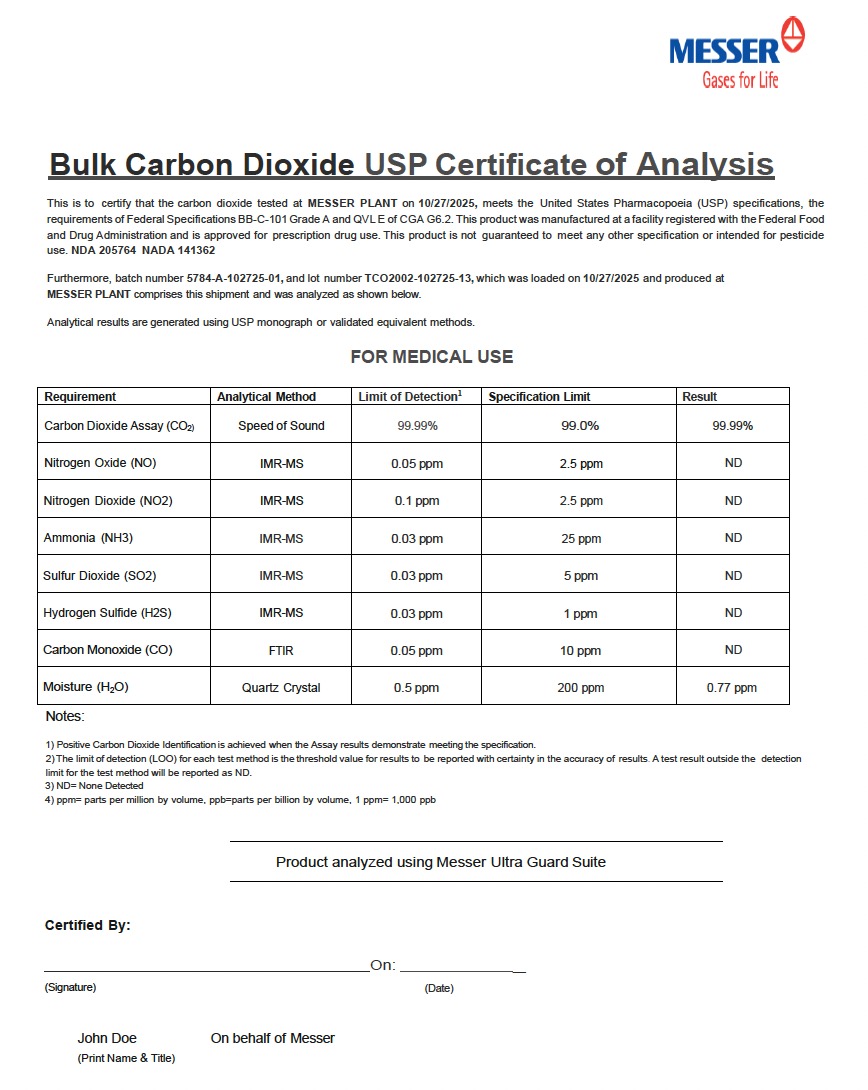 DRUG LABEL: Carbon Dioxide
NDC: 52374-103 | Form: GAS
Manufacturer: MESSER GAS PUERTO RICO, INC
Category: prescription | Type: HUMAN PRESCRIPTION DRUG LABEL
Date: 20260113

ACTIVE INGREDIENTS: CARBON DIOXIDE 990 mL/1 L

Carbon Dioxide Refrigerated Liquid USP

PACKAGE LABEL

Bulk Carbon Dioxide USP Certificate of Analysis
This is to certify that the carbon dioxide tested at MESSER PLANT on 10/27/2025, meets the United States Pharmacopoeia (USP) specifications, the requirements of Federal Specifications BB-C-101 Grade A and QVL E of CGA G6.2. This product was manufactured at a facility registered with the Federal Food and Drug Administration and is approved for prescription drug use. This product is not guaranteed to meet any other specification or intended for pesticide use. NDA 205764 NADA 141362
Furthermore, batch number 5784-A-102725-01, and lot number TCO2002-102725-13, which was loaded on 10/27/2025 and produced at MESSER PLANT comprises this shipment and was analyzed as shown below.
Analytical results are generated using USP monograph or validated equivalent methods.
FOR MEDICAL USE
Requirement Analytical Method Limit of Detection¹ Specification Limit Result
Carbon Dioxide Assay (CO₂) Speed of Sound 99.99% 99.0% 99.99%
Nitrogen Oxide (NO) IMR-MS 0.05 ppm 2.5 ppm ND
Nitrogen Dioxide (NO₂) IMR-MS 0.1 ppm 2.5 ppm ND
Ammonia (NH₃) IMR-MS 0.03 ppm 25 ppm ND
Sulfur Dioxide (SO₂) IMR-MS 0.03 ppm 5 ppm ND
Hydrogen Sulfide (H₂S) IMR-MS 0.03 ppm 1 ppm ND
Carbon Monoxide (CO) FTIR 0.05 ppm 10 ppm ND
Moisture (H₂O) Quartz Crystal 0.5 ppm 200 ppm 0.77 ppm
Notes:
1. Positive Carbon Dioxide Identification is achieved when the Assay results demonstrate meeting the specification.
2. The limit of detection (LOO) for each test method is the threshold value for results to be reported with certainty in the accuracy of results. A test result outside the detection limit for the test method will be reported as ND.
3. ND = None Detected
4. ppm = parts per million by volume, ppb = parts per billion by volume, 1 ppm = 1,000 ppb
Product analyzed using Messer Ultra Guard Suite
Certified By:
On:
(Signature) (Date)
John Doe
(Print Name & Title)
On behalf of Messer